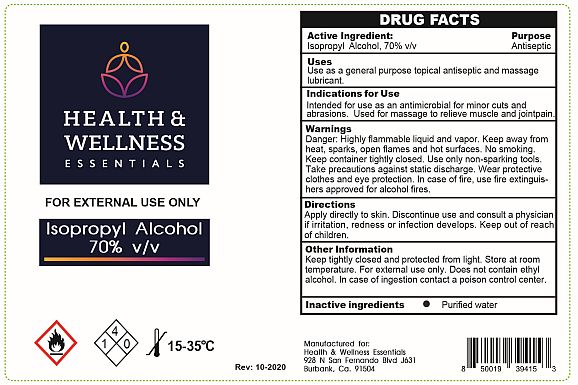 DRUG LABEL: Isopropyl Alcohol
NDC: 12745-106 | Form: LIQUID
Manufacturer: Medical Chemical Corporation
Category: otc | Type: HUMAN OTC DRUG LABEL
Date: 20220117

ACTIVE INGREDIENTS: ISOPROPYL ALCOHOL 70.14 g/100 mL
INACTIVE INGREDIENTS: WATER

ISOPROPYL ALCOHOL HEALTH AND WELLNESS

Purpose

Antiseptic

Uses

Use as a general purpose topical antiseptic and massage lubricant.

Active Ingredient

Isopropyl Alcohol, 70%

Directions

Apply directly to skin. Discontinue use and consult a physician if irritation, redness or infection develops. Keep out of reach of children.

Warnings

Danger: Highly flammable liquid and vapor. Keep away from heat, sparks, open flames and hot surfaces. No smoking. Keep container tightly closed. Use only non-sparking tools. Take precautions against static discharge. Wear protective clothes and eye protection. In case of fire, use fire extinguishers approved for alcohol fires.

Other Information

Keep tightly closed and protected from light. Store at room temperature. For external use only. Does not contain ethyl alcohol. In case of ingestion contact a poison control center.

Inactive Ingredients: Water

DOSAGE AND ADMINISTRATION

Directions: Apply to affected area for first-aid treatment of minor cuts and abrasions. In case of deep or puncture wounds consult a physician. Discontinue use and get medical aid if redness, irritation or infection develops. Apply liberally for rubbing.

PACKAGE LABEL

ipa70label.jpg